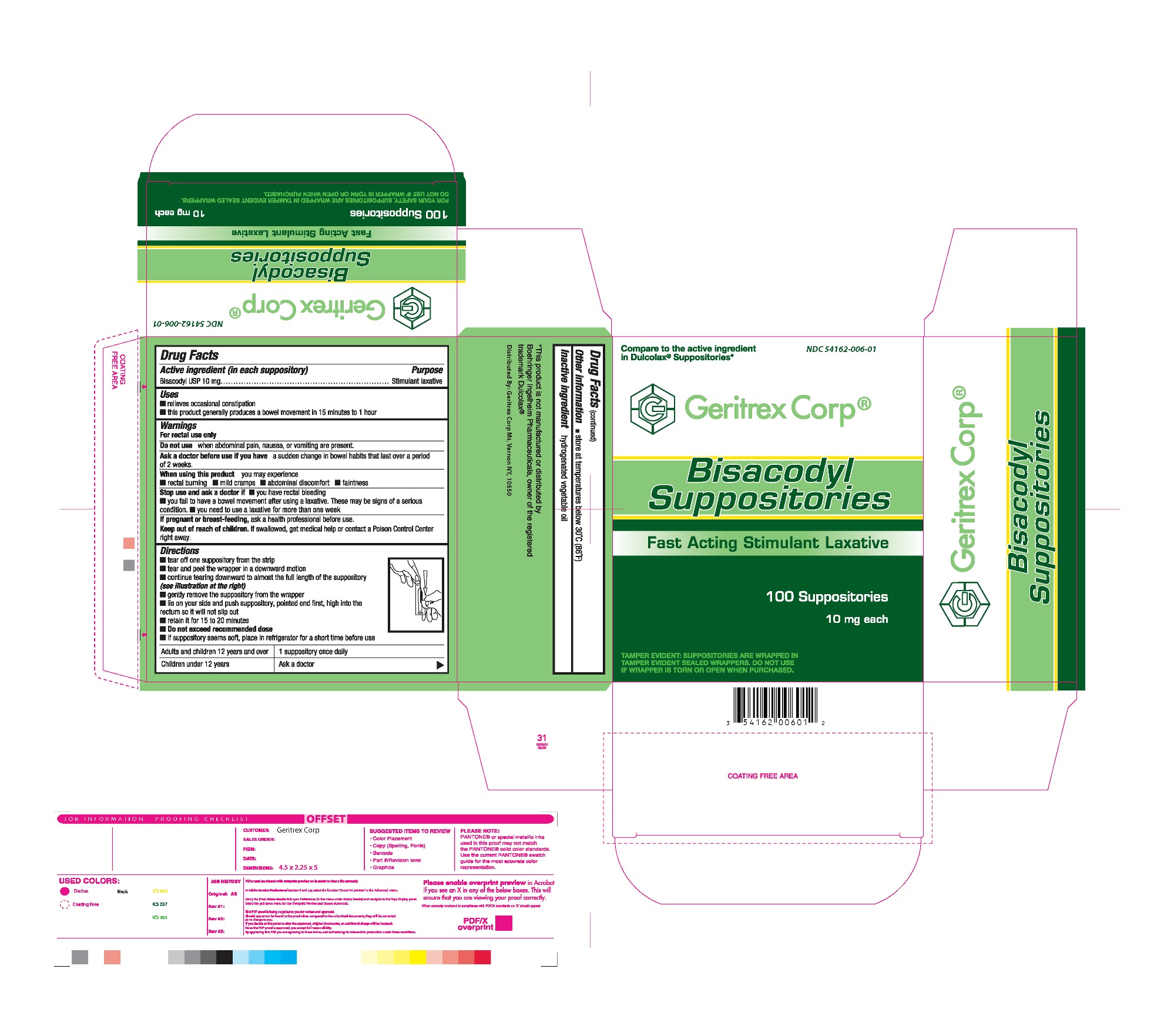 DRUG LABEL: BISACODYL
NDC: 54162-006 | Form: SUPPOSITORY
Manufacturer: Geritrex LLC
Category: otc | Type: HUMAN OTC DRUG LABEL
Date: 20160107

ACTIVE INGREDIENTS: BISACODYL 0.01 g/2 g
INACTIVE INGREDIENTS: HYDROGENATED SOYBEAN OIL

Bisacodyl Suppositories

Drug Facts

Active ingredient (in each suppository) Purpose

Bisacodyl USP 10 mg ................................ Stimulant laxative

Uses

relieves occasional constipation.

this product generally produces a bowel movement in 15 minutes to 1 hour.

Directions

tear off one suppository from the strip.
tear and peel the wrapper in downward motion.
continue tearing downward to almost the full length of the suppository (see illustration at the right)
gently remove the suppository from the wrapper.
lie on your side and push suppository. with pointed end first, high into the rectum so it will not slip out
retain it for 15 to 20 minutes.
Do not exceed recommended dose
if suppository seems soft, place in refrigerator for a short time before use
Adults and children 12 years and over 1 suppository once daily.
Children under 12 years Ask a doctor.

DOSAGE AND ADMINISTRATION

Adults and children 12 years and over 1 suppository once daily.
Children under 12 years Ask a doctor.

WARNINGS

For rectal use only.

Do not use when abdominal pain, nausea, or vomiting are present.

Ask a doctor before use if you have a sudden change in bowel habits that lasts over a period of 2 weeks.

When using this product you may experience. rectal burning. mild cramps.abdominal discomfort. faintness.

stop use and ask a doctor if you have rectal bleeding. you fill to have a bowel movement after using a laxative. These may be signs of a serious condition.

you need to use a laxative for more than one week.

if pregnant or breast-feeding, ask a health professional before use.

INACTIVE INGREDIENT

hydrogenated vegetable oil

STORAGE

store at temperatures below 30'C (86'F)

OTC - KEEP OUT OF REACH OF CHILDREN

If swallowed, get medical help or contact a poison control center right away.